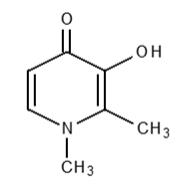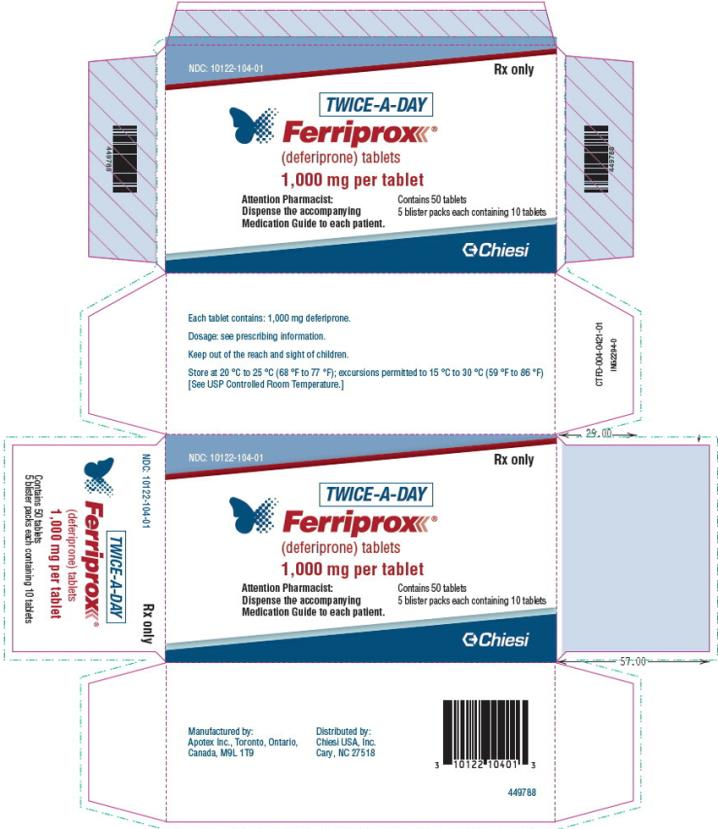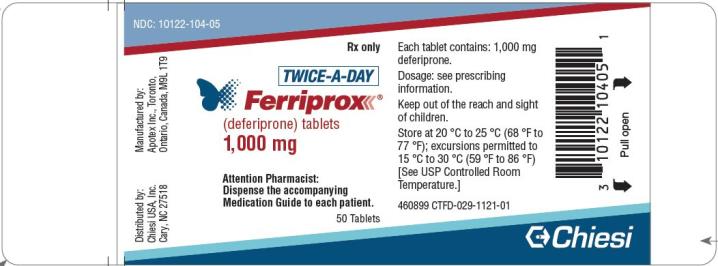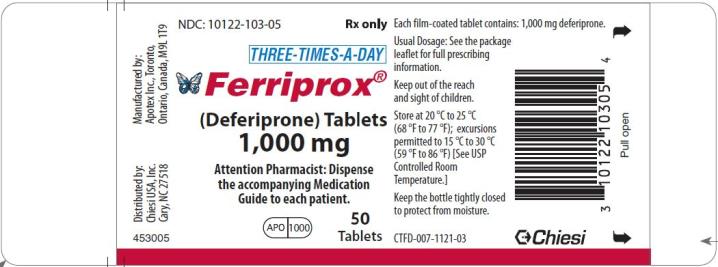 DRUG LABEL: FERRIPROX
NDC: 10122-104 | Form: TABLET
Manufacturer: Chiesi USA, Inc.
Category: prescription | Type: HUMAN PRESCRIPTION DRUG LABEL
Date: 20260128

ACTIVE INGREDIENTS: DEFERIPRONE 1000 mg/1 1
INACTIVE INGREDIENTS: MAGNESIUM STEARATE; TITANIUM DIOXIDE; MAGNESIUM OXIDE; SILICON DIOXIDE; TRIETHYL CITRATE; TALC; METHACRYLIC ACID AND ETHYL ACRYLATE COPOLYMER; HYPROMELLOSE ACETATE SUCCINATE 06081224 (3 MM2/S)

HIGHLIGHTS OF PRESCRIBING INFORMATION

These highlights do not include all the information needed to use FERRIPROX Tablets safely and effectively. See full prescribing information for FERRIPROX Tablets.
FERRIPROX® (deferiprone) tablets, for oral use
Initial U.S. Approval: 2011

RECENT MAJOR CHANGES

Warnings and Precautions, Agranulocytosis and Neutropenia (5.1) | 3/2025

WARNING: AGRANULOCYTOSIS AND NEUTROPENIA

See full prescribing information for complete boxed warning.

• FERRIPROX can cause agranulocytosis that can lead to serious infections and death. Neutropenia may precede the development of agranulocytosis. (5.1)

• Measure the absolute neutrophil count (ANC) before starting FERRIPROX and monitor regularly while on therapy. (5.1)

• Interrupt FERRIPROX therapy if neutropenia develops. (5.1)

• Interrupt FERRIPROX if infection develops and monitor the ANC more frequently. (5.1)

• Advise patients taking FERRIPROX to report immediately any symptoms indicative of infection. (5.1)

1 INDICATIONS AND USAGE

FERRIPROX Tablets are an iron chelator indicated for the treatment of transfusional iron overload in adult and pediatric patients 8 years of age and older with thalassemia syndromes, sickle cell disease or other anemias. (1)

Limitations of Use

Safety and effectiveness have not been established for the treatment of transfusional iron overload in patients with myelodysplastic syndrome or in patients with Diamond Blackfan anemia.

2 DOSAGE AND ADMINISTRATION

- FERRIPROX Tablets are available in two different 1,000 mg formulations, which have different dosing regimens to achieve the same total daily dosage. (2.1)
- To prevent medication errors, before prescribing and dispensing, ensure that the tablet formulation is appropriate for the dosing regimen. Each tablet has distinct identifying characteristics. (2.1, 3)
- FERRIPROX Tablets (twice a day), 1,000 mg:
  • Starting oral dosage: 75 mg/kg/day (actual body weight) in two divided doses (2.2)
  • Maximum oral dosage: 99 mg/kg/day (actual body weight) in two divided doses (2.2)
- FERRIPROX Tablets (three times a day), 1,000 mg:
  ○ Starting oral dosage: 75 mg/kg/day (actual body weight) in three divided doses (2.2)
  ○ Maximum oral dosage: 99 mg/kg/day (actual body weight) in three divided doses (2.2)

3 DOSAGE FORMS AND STRENGTHS

- Tablets (twice a day): 1,000 mg with functional scoring (3)
- Tablets (three times a day): 1,000 mg with functional scoring (3)

4 CONTRAINDICATIONS

Hypersensitivity to deferiprone or to any of the excipients in the formulations. (4)

5 WARNINGS AND PRECAUTIONS

- Liver Enzyme Elevations: Monitor monthly and discontinue for persistent elevations. (5.2)
- Zinc Deficiency: Monitor during therapy and supplement for deficiency. (5.3)
- Embryo-Fetal Toxicity: Can cause fetal harm. (5.4)

6 ADVERSE REACTIONS

- The most common adverse reactions in patients with thalassemia (incidence ≥ 6%) are nausea, vomiting, abdominal pain, arthralgia, ALT increased and neutropenia. (6)
- The most common adverse reactions in patients with sickle cell disease or other anemias (incidence ≥6%) are pyrexia, abdominal pain, bone pain, headache, vomiting, pain in extremity, sickle cell anemia with crisis, back pain, ALT increased, AST increased, arthralgia, oropharyngeal pain, nasopharyngitis, neutrophil count decreased, cough and nausea. (6)

To report SUSPECTED ADVERSE REACTIONS, contact Chiesi USA, Inc. at 1-888-661-9260 or FDA at 1-800-FDA-1088 or www.fda.gov/medwatch

7 DRUG INTERACTIONS

- Drugs Associated with Neutropenia or Agranulocytosis: Avoid co-administration. If co-administration is unavoidable, closely monitor the absolute neutrophil count. (7.1)
- UGT1A6 Inhibitors: Avoid co-administration. (7.2)
- Polyvalent Cations: Allow at least a 4-hour interval between administration of FERRIPROX and drugs or supplements containing polyvalent cations (e.g., iron, aluminum, or zinc). (2.2, 7.2)

8 USE IN SPECIFIC POPULATIONS

- Lactation: Advise not to breastfeed. (8.2)

FULL PRESCRIBING INFORMATION

WARNING: AGRANULOCYTOSIS AND NEUTROPENIA

• FERRIPROX can cause agranulocytosis that can lead to serious infections and death. Neutropenia may precede the development of agranulocytosis. [see Warnings and Precautions (5.1)]

• Measure the absolute neutrophil count (ANC) before starting FERRIPROX therapy and monitor regularly while on therapy.

• Interrupt FERRIPROX therapy if neutropenia develops. [see Warnings and Precautions (5.1)]

• Interrupt FERRIPROX if infection develops, and monitor the ANC more frequently. [see Warnings and Precautions (5.1)]

• Advise patients taking FERRIPROX to report immediately any symptoms indicative of infection. [see Warnings and Precautions (5.1)]

1 INDICATIONS AND USAGE

FERRIPROX Tablets are indicated for the treatment of transfusional iron overload in adult and pediatric patients 8 years of age and older with thalassemia syndromes, sickle cell disease or other anemias.

Limitations of Use

• Safety and effectiveness have not been established for the treatment of transfusional iron overload in patients with myelodysplastic syndrome or in patients with Diamond Blackfan anemia.

2 DOSAGE AND ADMINISTRATION

2.1 Important Dosage and Administration Information

FERRIPROX Tablets are available in two different 1,000 mg formulations, which have different oral dosing regimens to achieve the same total daily dosage.

- FERRIPROX Tablets (twice a day) - 1,000 mg - given two times a day [see Dosage and Administration (2.2)]
- FERRIPROX Tablets (three times a day) - 1,000 mg - given three times a day [see Dosage and Administration (2.3)]

To prevent medication errors, before prescribing and dispensing, ensure that the tablet formulation is appropriate for the dosing regimen. Each tablet has distinct identifying characteristics [see Dosage Forms and Strengths (3)].

For patients who have trouble swallowing tablets, consider the use of FERRIPROX Oral Solution (see the prescribing information for FERRIPROX Oral Solution).

Monitoring for Safety

Due to the risk of agranulocytosis, monitor ANC before and during FERRIPROX therapy.

Test ANC prior to start of FERRIPROX therapy and monitor on the following schedule during treatment:

• First six months of therapy: Monitor ANC weekly;

• Next six months of therapy: Monitor ANC once every two weeks;

• After one year of therapy: Monitor ANC every two to four weeks (or at the patient’s blood transfusion interval in patients that have not experienced an interruption due to any decrease in ANC [see Warnings and Precautions (5.1)].

Due to the risk of hepatic transaminase elevations, monitor ALT before and monthly during FERRIPROX therapy [see Warnings and Precautions (5.2)].

Due to the risk of zinc deficiency, monitor zinc levels before and regularly during FERRIPROX therapy [see Warnings and Precautions (5.3)].

2.2 Recommended Dosage for 1,000 mg FERRIPROX Tablets (twice a day) for Adult and Pediatric Patients with Transfusional Iron Overload due to Thalassemia Syndromes, Sickle Cell Disease or Other Anemias

Starting Dosage for Twice a Day Tablets

The recommended starting oral dosage of FERRIPROX Tablets (twice a day) is 75 mg/kg/day (actual body weight) in two divided doses per day (taken approximately 12 hours apart), with food. Round the total daily dose to the nearest 500 mg (half-tablet). Table 1 describes the number of FERRIPROX Tablets (twice a day) needed to achieve the 75 mg/kg/day total starting daily dosage.

Table 1: Number of FERRIPROX 1,000 mg Tablets (twice a day) Needed to Achieve the Total Starting Daily Dosage of 75 mg/kg (rounded to the nearest half-tablet)
Body Weight (kg) | Morning | Evening
20 | 0.5 | 1
30 | 1 | 1.5
40 | 1.5 | 1.5
50 | 2 | 2
60 | 2 | 2.5
70 | 2.5 | 3
80 | 3 | 3
90 | 3.5 | 3.5

To minimize gastrointestinal upset when first starting therapy, dosing can start at 45 mg/kg/day and increase weekly by 15 mg/kg/day increments until the full prescribed dose is achieved.

Dosage Adjustments for Twice a Day Tablets

Tailor dosage adjustments of FERRIPROX Tablets (twice a day) to the individual patient’s response and therapeutic goals (maintenance or reduction of body iron burden). The maximum total daily oral dosage is 99 mg/kg (actual body weight) divided into two doses taken approximately 12 hours apart with food. Table 2 describes the number of FERRIPROX Tablets (twice a day) needed to achieve the 99 mg/day total maximum daily dosage.

Table 2: Number of FERRIPROX 1,000 mg Tablets (twice a day) Needed to Achieve a Total Maximum Recommended Daily Dosage of 99 mg/kg (rounded to the nearest half-tablet)
Body Weight (kg) | Morning | Evening
20 | 1 | 1
30 | 1.5 | 1.5
40 | 2 | 2
50 | 2.5 | 2.5
60 | 3 | 3
70 | 3.5 | 3.5
80 | 4 | 4
90 | 4.5 | 4.5

2.3 Recommended Dosage for 1,000 mg FERRIPROX Tablets (three times a day) for Adult and Pediatric Patients with Transfusional Iron Overload due to Thalassemia Syndromes, Sickle Cell Disease or Other Anemias

Starting Dosage for Three Times a Day Tablets

The recommended starting oral dosage of FERRIPROX Tablets (three times a day) is 75 mg/kg/day (actual body weight), in three divided doses per day. Table 3 describes the number of FERRIPROX Tablets (three times a day) needed to achieve the 75 mg/kg/day total starting dosage). Round dose to the nearest 500 mg (half-tablet).

Table 3: Number of FERRIPROX 1,000 mg Tablets (three times a day) Needed to Achieve the Total Starting Daily Dosage of 75 mg/kg (rounded to the nearest half-tablet)
Body Weight (kg) | Morning | Midday | Evening
20 | 0.5 | 0.5 | 0.5
30 | 1 | 0.5 | 1
40 | 1 | 1 | 1
50 | 1.5 | 1 | 1.5
60 | 1.5 | 1.5 | 1.5
70 | 2 | 1.5 | 2
80 | 2 | 2 | 2
90 | 2.5 | 2 | 2.5

To minimize gastrointestinal upset when first starting therapy, dosing can start at 45 mg/kg/day and increase weekly by 15 mg/kg/day increments until the full prescribed dose is achieved.

Dosage Adjustments for Three Times Daily Tablets

Tailor dosage adjustments for FERRIPROX Tablets (three times a day) to the individual patient’s response and therapeutic goals (maintenance or reduction of body iron burden). The maximum oral dosage is 99 mg/kg/day (actual body weight), in three divided doses per day. Table 4 describes the number of FERRIPROX Tablets (three times a day) needed to achieve the 99 mg/day total maximum daily dosage.

Table 4: Number of FERRIPROX 1,000 mg Tablets (three times a day) Needed to Achieve the Maximum Total Daily Dosage of 99 mg/kg (rounded to the nearest half-tablet)
Body Weight (kg) | Morning | Midday | Evening
20 | 0.5 | 0.5 | 1
30 | 1 | 1 | 1
40 | 1.5 | 1 | 1.5
50 | 1.5 | 1.5 | 2
60 | 2 | 2 | 2
70 | 2.5 | 2 | 2.5
80 | 2.5 | 2.5 | 3
90 | 3 | 3 | 3

2.4 Monitoring Ferritin Levels to Assess Efficacy

Monitor serum ferritin concentration every two to three months to assess the effect of FERRIPROX on body iron stores. If the serum ferritin is consistently below 500 mcg/L, consider temporarily interrupting FERRIPROX therapy until serum ferritin rises above 500 mcg/L.

2.5 Dosage Modification for Drug Interactions

Allow at least a 4-hour interval between administration of FERRIPROX and other drugs or supplements containing polyvalent cations such as iron, aluminum, or zinc [see Drug Interactions (7.2), Clinical Pharmacology (12.3)].

3 DOSAGE FORMS AND STRENGTHS

- Tablets (twice a day): 1,000 mg, capsule-shaped, white to off-white tablets with functional scoring, engraved “FPX” bisect “DR” on one side, “APO” bisect “1000” on the other”.
- Tablets (three times a day): 1,000 mg film-coated, capsule-shaped, white to off-white tablets with functional scoring, and imprinted with “APO” score “1000” on one side and plain on the other.

4 CONTRAINDICATIONS

FERRIPROX is contraindicated in patients with known hypersensitivity to deferiprone or to any of the excipients in the formulations. The following reactions have been reported in association with the administration of deferiprone: Henoch-Schönlein purpura; urticaria; and periorbital edema with skin rash [see Adverse Reactions (6.2)].

5 WARNINGS AND PRECAUTIONS

5.1 Agranulocytosis and Neutropenia

Fatal agranulocytosis can occur with FERRIPROX use. FERRIPROX can also cause neutropenia, which may foreshadow agranulocytosis. Measure the absolute neutrophil count (ANC) before starting FERRIPROX therapy and monitor it regularly while on therapy [see Dosage and Administration (2.1)].

Reduction in the frequency of ANC monitoring should be considered on an individual patient basis, according to the health care provider’s assessment of the patient’s understanding of the risk minimization measures required during therapy.

Interrupt FERRIPROX therapy if neutropenia develops (ANC < 1.5 x 10^9/L).

Interrupt FERRIPROX if infection develops and monitor the ANC frequently.

Advise patients taking FERRIPROX to immediately interrupt therapy and report to their physician if they experience any symptoms indicative of infection.

The incidence of agranulocytosis was 1% of patients in pooled clinical trials of 642 patients with thalassemia syndromes and 0.5% of patients in pooled clinical trials of 196 patients with sickle cell disease or other anemias. The mechanism of FERRIPROX-associated agranulocytosis is unknown. Agranulocytosis and neutropenia usually resolve upon discontinuation of FERRIPROX, but there have been reports of agranulocytosis leading to death.

Implement a plan to monitor for and to manage agranulocytosis and neutropenia prior to initiating FERRIPROX treatment.

For agranulocytosis (ANC < 0.2 x 10^9/L) and severe neutropenia (0.2 x 10^9/L ≤ ANC < 0.5 x 10^9/L):

Consider hospitalization and other management as clinically appropriate.

Do not resume FERRIPROX in patients who have developed agranulocytosis unless potential benefits outweigh potential risks. Do not rechallenge patients who have developed neutropenia with FERRIPROX unless potential benefits outweigh potential risks.

For neutropenia (ANC < 1.5 x 10^9/L and ≥ 0.5 x 10^9/L):

Instruct the patient to immediately discontinue FERRIPROX and all other medications with a potential to cause neutropenia.

Obtain a complete blood cell (CBC) count, including a white blood cell (WBC) count corrected for the presence of nucleated red blood cells, an absolute neutrophil count (ANC), and a platelet count daily until recovery (ANC ≥ 1.5 x 10^9/L).

5.2 Liver Enzyme Elevations

In pooled clinical trials, 7.5% of 642 patients with thalassemia syndromes treated with FERRIPROX developed increased ALT values. Four (0.62%) FERRIPROX-treated subjects discontinued the drug due to increased serum ALT levels and 1 (0.16%) due to an increase in both ALT and AST. In pooled clinical trials, 7.7% of 196 patients with sickle cell disease or other anemias treated with FERRIPROX developed increased ALT values.

Monitor serum ALT values monthly during therapy with FERRIPROX and consider interruption of therapy if there is a persistent increase in the serum transaminase levels [see Dosage and Administration (2.1)].

5.3 Zinc Deficiency

Decreased plasma zinc concentrations have been observed on FERRIPROX therapy. Monitor plasma zinc annually, and supplement in the event of a deficiency [see Dosage and Administration (2.1)].

5.4 Embryo-Fetal Toxicity

Based on findings from animal reproduction studies and evidence of genotoxicity, FERRIPROX can cause fetal harm when administered to a pregnant woman. The available data on the use of FERRIPROX in pregnant women are insufficient to inform risk. In animal studies, administration of deferiprone during the period of organogenesis resulted in embryo-fetal death and malformations at doses lower than equivalent human clinical doses. Advise pregnant women and females of reproductive potential of the potential risk to the fetus [see Use in Specific Populations (8.1)].

Advise females of reproductive potential to use an effective method of contraception during treatment with FERRIPROX and for at least six months after the last dose. Advise males with female partners of reproductive potential to use effective contraception during treatment with FERRIPROX and for at least three months after the last dose [see Use in Specific Populations (8.1, 8.3)].

6 ADVERSE REACTIONS

The following clinically significant adverse reactions are described below and elsewhere in the labeling:

- Agranulocytosis and Neutropenia [see Warnings and Precautions (5.1)]
- Liver Enzyme Elevations [see Warnings and Precautions (5.2)]
- Zinc Deficiency [see Warnings and Precautions (5.3)]

6.1 Clinical Trial Experience

Because clinical trials are conducted under widely varying conditions, adverse reaction rates observed in the clinical trials of a drug cannot be directly compared to rates in the clinical trials of another drug and may not reflect the rates observed in practice.

FERRIPROX Tablets (twice a day) were evaluated in trials in healthy subjects. FERRIPROX Tablets (twice a day) contain deferiprone, the same active ingredient as FERRIPROX Tablets (deferiprone) (three times a day) and FERRIPROX Oral Solution (deferiprone).

The following adverse reaction information represents the pooled data collected from single arm or active-controlled clinical trials with FERRIPROX Tablets (deferiprone) (three times a day) or FERRIPROX Oral Solution (deferiprone).

Thalassemia Syndromes

The safety of FERRIPROX was evaluated in the pooled clinical trial database [see Clinical Studies (14.1)]. Patients received FERRIPROX Tablets (three times a day) or FERRIPROX Oral Solution . FERRIPROX was administered orally three times a day (total daily dose either 50, 75, or 99 mg/kg), N=642. Among 642 patients receiving FERRIPROX, 492 (76.6%) were exposed for 6 months or longer and 365 (56.9%) were exposed for greater than one year.

The median age of patients who received FERRIPROX was 19 years (range 1, 77 years); 50.2% female; 71.2% White, 17.8% Asian, 9.2% Unknown, 1.2% Multi-racial and 0.6% Black.

The most serious adverse reaction reported in clinical trials with FERRIPROX was agranulocytosis [see Warnings and Precautions (5.1)].

The most common adverse reactions (≥6%) reported during clinical trials were nausea, vomiting, abdominal pain, arthralgia, alanine aminotransferase increased and neutropenia.

The table below lists the adverse drug reactions that occurred in at least 1% of patients treated with FERRIPROX in clinical trials in patients with thalassemia syndromes.

Table 5: Adverse reactions occurring in ≥ 1% of FERRIPROX-treated patients with thalassemia syndromes
Body System | (N=642)
Adverse Reaction | % Patients
BLOOD AND LYMPHATIC SYSTEM DISORDERS
Neutropenia* | 7
Agranulocytosis† | 1
GASTROINTESTINAL DISORDERS
Nausea | 13
Abdominal pain/discomfort | 10
Vomiting | 10
Diarrhea | 3
Dyspepsia | 2
INVESTIGATIONS
Alanine aminotransferase increased | 7
Weight increased | 2
Aspartate aminotransferase increased | 1
METABOLISM AND NUTRITION DISORDERS
Increased appetite | 4
Decreased appetite | 1
MUSCULOSKELETAL AND CONNECTIVETISSUE DISORDERS
Arthralgia | 10
Back pain | 2
Pain in extremity | 2
Arthropathy | 1
NERVOUS SYSTEM DISORDERS
Headache | 2
*Neutropenia includes events of severe neutropenia (ANC ≥0.2 x 10^9/L and <0.5 x 10^9/L).
†Agranulocytosis (ANC< 0.2 x 10^9/L)

Gastrointestinal symptoms such as nausea, vomiting, and abdominal pain were the most frequent adverse reactions reported by patients participating in clinical trials and led to the discontinuation of FERRIPROX therapy in 1.6% of patients.

Chromaturia (reddish/brown discoloration of the urine) is a result of the excretion of iron in the urine.

Sickle Cell Disease or Other Anemias

The safety of FERRIPROX compared to deferoxamine was evaluated in LA38-0411 [see Clinical Studies (14.2)]. Patients received FERRIPROX Tablets or FERRIPROX Oral Solution orally three times a day (total daily dose 75-99 mg/kg/day) n=152) or the control arm, deferoxamine, 20-40 mg/kg/day (children) or 40-50 mg/kg/day (adults), by subcutaneous infusion for 5 – 7 days per week, n=76. Among 152 patients receiving FERRIPROX, 120 (78.9%) were exposed for 6 months or longer and 17 (11.2%) were exposed for greater than one year.

The median age of patients who received FERRIPROX was 15 years (range 3, 59 years); 54.6% male; 78.9% White, 15.1% Black and 5.9% Multi-racial.

The most common adverse reactions (≥6%) reported during clinical trials in patients with SCD or other anemias were pyrexia, abdominal pain, bone pain, headache, vomiting, pain in extremity, sickle cell anemia with crisis, back pain, alanine aminotransferase (ALT) increased, aspartate aminotransferase (AST) increased, arthralgia, oropharyngeal pain, nasopharyngitis, neutrophil count decreased, cough and nausea.

The table below lists the adverse reactions (irrespective of a causal assessment; adverse events) of interest that occurred in patients treated with FERRIPROX in clinical trials in subjects with sickle cell disease or other anemias.

Table 6: Adverse reactions occurring in ≥5% of FERRIPROX-treated patients with sickle cell disease or other anemias
Body System Adverse Reaction | FERRIPROX (N=152) % Patients | DEFEROXAMINE (N=76) % Patients
BLOOD AND LYMPHATIC SYSTEM DISORDERS
Sickle cell anemia with crisis | 17 | 13
GASTROINTESTINAL DISORDERS
Abdominal pain* | 26 | 13
Vomiting | 19 | 11
Nausea | 7 | 9
Diarrhea | 5 | 8
GENERAL DISORDERS AND ADMINISTRATION SITE CONDITIONS
Pyrexia | 28 | 33
Pain | 5 | 4
INFECTIONS AND INFESTATIONS
Nasopharyngitis | 9 | 12
Upper respiratory tract infection | 5 | 3
INVESTIGATIONS
Alanine aminotransferase increased | 12 | 0
Aspartate aminotransferase increased | 11 | 0
Neutrophil count decreased | 8 | 4
MUSCULOSKELETAL AND CONNECTIVE TISSUE DISORDERS
Bone pain | 25 | 34
Pain in extremity | 18 | 15
Back pain | 13 | 18
Arthralgia | 10 | 8
NERVOUS SYSTEM DISORDERS
Headache | 20 | 13
RESPIRATORY, THORACIC AND MEDIASTINAL DISORDERS
Oropharyngeal pain | 10 | 15
Cough | 8 | 15

*Grouped term

Clinically relevant adverse reactions in <5% of patients include neutropenia and agranulocytosis.

Pediatric Patients

FERRIPROX has been studied in 86 pediatric patients with sickle cell disease or other anemias. Pediatric patients (<17 years) had an increase in the following adverse reactions as compared to adults: abdominal pain, neutrophil count decreased, bone pain and oropharyngeal pain.

6.2 Postmarketing Experience

The following additional adverse reactions have been reported in patients receiving FERRIPROX. Because these reactions are reported voluntarily from a population of uncertain size, it is not always possible to reliably estimate their frequency or to establish a causal relationship to drug exposure.

Blood and lymphatic system disorders: thrombocytosis, pancytopenia.

Cardiac disorders: atrial fibrillation, cardiac failure.

Congenital, familial and genetic disorders: hypospadias.

Eye disorders: diplopia, papilledema, retinal toxicity.

Gastrointestinal disorders: enterocolitis, rectal hemorrhage, gastric ulcer, pancreatitis, parotid gland enlargement.

General disorders and administration site conditions: chills, edema peripheral, multi-organ failure.

Hepatobiliary disorders: jaundice, hepatomegaly.

Immune system disorders: anaphylactic shock, hypersensitivity.

Infections and infestations: cryptococcal cutaneous infection, enteroviral encephalitis, pharyngitis, pneumonia, sepsis, furuncle, infectious hepatitis, rash pustular, subcutaneous abscess.

Investigations: blood bilirubin increased, blood creatinine phosphokinase increased.

Metabolism and nutrition disorders: metabolic acidosis, dehydration.

Musculoskeletal and connective tissue disorders: myositis, chondropathy, trismus.

Nervous system disorders: cerebellar syndrome, cerebral hemorrhage, convulsion, gait disturbance, intracranial pressure increased, psychomotor skills impaired, pyramidal tract syndrome, somnolence.

Psychiatric disorders: bruxism, depression, obsessive-compulsive disorder.

Renal disorders: glycosuria, hemoglobinuria.

Respiratory, thoracic and mediastinal disorders: acute respiratory distress syndrome, epistaxis, hemoptysis, pulmonary embolism.

Skin, subcutaneous tissue disorders: hyperhidrosis, periorbital edema, photosensitivity reaction, pruritis, urticaria, rash, Henoch-Schönlein purpura.

Vascular disorders: hypotension, hypertension.

7 DRUG INTERACTIONS

7.1 Drugs Associated with Neutropenia or Agranulocytosis

Avoid co-administration of FERRIPROX with other drugs known to be associated with neutropenia or agranulocytosis. If co-administration is unavoidable, closely monitor the absolute neutrophil count [see Warnings and Precautions (5.1)].

7.2 Effect of Other Drugs on FERRIPROX

UDP-Glucuronosyltransferases (UGT)

Avoid use of UGT1A6 inhibitors (e.g., diclofenac, probenecid, or silymarin (milk thistle)) with FERRIPROX [see Dosage and Administration (2.2), Adverse Reactions (6.1), Clinical Pharmacology (12.3)].

Polyvalent Cations

Deferiprone has the potential to bind polyvalent cations (e.g., iron, aluminum, and zinc); allow at least a 4-hour interval between FERRIPROX and other medications (e.g., antacids), or supplements containing these polyvalent cations [see Dosage and Administration (2.2)].

8 USE IN SPECIFIC POPULATIONS

8.1 Pregnancy

Risk Summary

In animal reproduction studies, oral administration of deferiprone to pregnant rats and rabbits during organogenesis at doses 33% and 49%, respectively, of the maximum recommended human dose (MRHD) resulted in structural abnormalities, embryo-fetal mortality and alterations to growth (see Data). The limited available data from deferiprone use in pregnant women are insufficient to inform a drug-associated risk of major birth defects and miscarriage. Based on evidence and developmental toxicity in animal studies, FERRIPROX can cause fetal harm when administered to a pregnant woman. Advise pregnant women and females of reproductive potential of the potential risk to a fetus.

The estimated background risk of major birth defects and miscarriage for the indicated population is unknown. All pregnancies have a background risk of birth defect, loss, or other adverse outcomes. In the U.S. general population, the estimated background risk of major birth defects and of miscarriage is 2-4% and 15-20%, respectively.

Data

Human Data

Post-marketing data available from 39 pregnancies of deferiprone-treated patients and 10 pregnancies of partners of deferiprone-treated patients are as follows:

Of the 39 pregnancies in deferiprone-treated patients, 23 resulted in healthy newborns, 6 ended in spontaneous abortion, 9 had unknown outcomes, and 1 infant was born with anal atresia, nephroptosis, ventricular septal defect, hemivertebra and urethral fistula.

Of the 10 pregnancies in partners of deferiprone-treated patients, 5 resulted in healthy newborns, 1 resulted in a healthy newborn with slight hypospadias, 1 was electively terminated, 1 resulted in the intrauterine death of twins, and 2 had unknown outcomes.

Animal Data

During organogenesis, pregnant rats and rabbits received deferiprone at oral doses of 0, 30, 80 or 200 mg/kg/day, and 0, 10, 50, or 150 mg/kg/day, respectively. The daily dose was administered as two equal divided doses approximately 7 hours apart. Doses of 200 mg/kg/day in rats and 150 mg/kg/day in rabbits, approximately 33% and 49% of the MRHD, respectively, resulted in increased post-implantation loss and reduced fetal weights in the presence of maternal toxicity (reduced maternal body weight and body weight gain in both rats and rabbits; abnormal large placenta at low incidence in rats). The 200 mg/kg/day dose in rats resulted in external, visceral and skeletal fetal malformations such as cranial malformations, cleft palate, limb malrotation, anal atresia, internal hydrocephaly, anophthalmia and fused bones. The dose of 150 mg/kg/day in rabbits resulted in external fetal malformations (partially opened eyes) and minor blood vessel and skeletal variations.

In rats, malformations including micrognathia and persistent ductus arteriosus could be observed in the absence of maternal toxicity at doses equal to or greater than 30 and 80 mg/kg/day, approximately 5% and 13% of the MHRD, respectively.

8.2 Lactation

Risk Summary

There is no information regarding the presence of deferiprone in human milk, the effects on the breastfed child, or the effects on milk production.

Because of the potential for serious adverse reactions in the breastfed child, including the potential for tumorigenicity shown for deferiprone in animal studies, advise patients that breastfeeding is not recommended during treatment with FERRIPROX, and for at least 2 weeks after the last dose.

8.3 Females and Males of Reproductive Potential

Pregnancy Testing

Pregnancy testing is recommended for females of reproductive potential prior to initiating FERRIPROX.

Contraception

Females

FERRIPROX can cause embryo-fetal harm when administered to a pregnant woman [see Use in Specific Populations (8.1)]. Advise female patients of reproductive potential to use effective contraception during treatment with FERRIPROX and for at least 6 months after the last dose.

Males

Based on genotoxicity findings, advise males with female partners of reproductive potential to use effective contraception during treatment with FERRIPROX and for at least 3 months after the last dose [see Nonclinical Toxicology (13.1)].

8.4 Pediatric Use

The safety and effectiveness of FERRIPROX for the treatment of transfusional iron overload due to thalassemia syndromes have been established in pediatric patients 8 years of age and older. Use of FERRIPROX for this indication is supported by evidence of efficacy from clinical trials in adult patients with thalassemia and evidence of safety in pediatric patients with sickle cell disease.

The safety and effectiveness of FERRIPROX for the treatment of transfusional iron overload due to sickle cell disease or other anemias have been established in 86 pediatric patients 3 to 16 years of age, among the 152 patients treated with FERRIPROX Tablets or Oral Solution in an adequate and well-controlled study [see Adverse Reactions (6.1) and Clinical Studies (14.2)]. The study included 56 patients 3 to <12 years of age and 30 patients 12 to 16 years of age. Seventy-six percent of these patients had sickle cell disease. The recommended starting dose and dose-modifications are the same for children and adults [see Indications and Usage (1), Dosage and Administration (2.1), and Clinical Studies (14)].

Fourteen patients with spherocytosis (including hereditary) (ages 3-15), two patients with pyruvate kinase deficiency (ages 4 and 6), two patients with dyserythropoietic anemia (ages 10-12) and two patients with hemolytic anemia (ages 8 and 10 years old) were treated with FERRIPROX in the clinical trial, LA38-0411.

A US registry established from December 2011 through December 2019, contains 125 patients from 4 to < 17 years old who have received FERRIPROX and have sickle cell disease. The adverse reactions, including agranulocytosis, seen in the 8 year period of the registry are similar to those seen in the most recent clinical studies.

Safety and effectiveness of FERRIPROX Tablets have not been established in pediatric patients with chronic iron overload due to blood transfusions who are less than 8 years of age.

8.5 Geriatric Use

Clinical studies of deferiprone did not include sufficient numbers of subjects aged 65 and over to determine whether they respond differently from younger subjects. Other reported clinical experience has not identified differences in responses between the elderly and younger patients.

10 OVERDOSAGE

No cases of acute overdose have been reported. There is no specific antidote to FERRIPROX overdose.

Neurological disorders such as cerebellar symptoms, diplopia, lateral nystagmus, psychomotor slowdown, hand movements and axial hypotonia have been observed in children treated with 2.5 to 3 times the recommended dose for more than one year. The neurological disorders progressively regressed after deferiprone discontinuation.

11 DESCRIPTION

FERRIPROX Tablets (deferiprone) contain 1,000 mg deferiprone (3-hydroxy-1,2-dimethylpyridin-4-one), a synthetic, orally active, iron-chelating agent. The molecular formula for deferiprone is C7H9NO2 and its molecular weight is 139.15 g/mol. Deferiprone has the following structural formula:

Deferiprone is a white to pinkish-white powder. It is sparingly soluble in deionized water (14.3 mg/mL) and has a melting point range of 272 °C - 278 °C.

FERRIPROX Tablets (twice a day), 1,000 mg

White to off-white, capsule-shaped tablets, and imprinted with “FPX” score “DR” on one side and “APO” score “1000” on the other. The tablets can be broken in half along the score line. Each tablet contains 1,000 mg deferiprone and the following inactive ingredients: Tablet core - hypromellose acetate succinate, magnesium oxide, colloidal silicon dioxide and magnesium stearate; Coating - triethyl citrate, talc, titanium dioxide, and methacrylic acid and ethyl acrylate copolymer.

FERRIPROX Tablets (three times a day), 1,000 mg

White to off-white, capsule-shaped tablets, and imprinted with “APO” score “1000” on one side and plain on the other. The tablets can be broken in half along the score line. Each tablet contains 1,000 mg deferiprone and the following inactive ingredients: Tablet core - methylcellulose, crospovidone, and magnesium stearate; Coating - hypromellose, hydroxypropyl cellulose, macrogol, and titanium dioxide.

12 CLINICAL PHARMACOLOGY

12.1 Mechanism of Action

Deferiprone is a chelating agent with an affinity for ferric ions (iron III). Deferiprone binds with ferric ions to form neutral 3:1 (deferiprone:iron) complexes that are stable at physiological pH.

12.2 Pharmacodynamics

No clinical studies were performed to assess the relationship between the dose of deferiprone and the amount of iron eliminated from the body.

Cardiac Electrophysiology

At the maximum approved recommended dose, deferiprone does not prolong the QT interval to any clinically relevant extent.

12.3 Pharmacokinetics

FERRIPROX Tablets (twice a day), 1,000 mg

In healthy subjects, the mean ± SD Cmax of deferiprone in serum was 6 ± 2 mcg/mL, and the mean ± SD AUC was 28 ± 7 mcg∙h/mL following oral administration of a 1,000 mg dose of FERRIPROX Tablets (twice a day) with food.

Absorption

Peak serum concentrations of deferiprone occur approximately 2 hours after a single dose of FERRIPROX Tablets (twice a day) in fasted healthy subjects.

Effect of Food

Following the administration of FERRIPROX Tablets (twice a day) to healthy volunteers, the Cmax and the AUC of deferiprone remain unchanged after a high-fat meal (approximately 1,000 calories, 53% fat, 33% carbohydrates, and 14% protein) compared to fasted conditions.

Effect of Alcohol

At 40% (v/v) alcohol concentration in vitro dissolution studies, there was 88% release of deferiprone from a 1,000 mg FERRIPROX tablet (twice a day) within two hours compared to 4% release of deferiprone within 2 hours in the absence of alcohol.

Distribution

The apparent mean ± SD volume of distribution (V/F) of deferiprone was 97 ± 28 L following oral administration of a 1,000 mg dose of FERRIPROX Tablets (twice a day) with food.

Elimination

The mean ± SD elimination half-life of deferiprone is 1.8 ± 0.3 hours following the administration of FERRIPROX Tablets (twice a day).

Metabolism

Deferiprone is metabolized primarily by UGT1A6. The major metabolite of deferiprone is the 3-O-glucuronide, which lacks iron- binding capability.

Excretion

Following oral administration, 75% to 90% of the administered dose was recovered in urine (primarily as metabolite) in the first 24 hours.

FERRIPROX Tablets (three times a day), 1,000 mg

The mean Cmax and AUC of deferiprone was 20 mcg/mL and 50 mcg∙h/mL, respectively, in healthy subjects. The dose proportionality of deferiprone over the approved recommended dosage range is unknown.

Absorption

Deferiprone appeared in the blood within 5 to 10 minutes after oral administration. Peak serum concentration of deferiprone was reached approximately 1 to 2 hours after a single dose.

Effect of Food

No clinically significant differences in the pharmacokinetics of deferiprone were observed following administration with food.

Elimination

The elimination half-life of deferiprone is approximately 2 hours.

Metabolism

Deferiprone is metabolized primarily by UGT1A6. The major metabolite of deferiprone is the 3-O-glucuronide, which lacks iron binding capability.

Excretion

Following oral administration, 75% to 90% of the administered dose was recovered in urine (primarily as metabolite) in the first 24 hours.

Specific Populations

No clinically significant differences in the pharmacokinetics of deferiprone were observed based on sex, race/ethnicity, body weight, mild to severe (eGFR 15 to 89 mL/min/1.73 m^2) renal impairment, or mild (Child Pugh Class A) to moderate (Child Pugh Class B) hepatic impairment. The effect of age, including geriatric or pediatric populations, end stage renal disease or severe (Child Pugh Class C) hepatic impairment on the pharmacokinetics of deferiprone is unknown.

Drug Interaction Studies

In Vitro Studies

UGTIA6 Inhibitors: Phenylbutazone (UGT1A6 inhibitor) decreased glucuronidation of deferiprone by up to 78%.

Polyvalent Cations: Deferiprone has the potential to bind polyvalent cations (e.g., iron, aluminum, and zinc).

13 NONCLINICAL TOXICOLOGY

13.1 Carcinogenesis, Mutagenesis, Impairment of Fertility

Carcinogenicity studies have not been conducted with deferiprone. However, in view of the genotoxicity results, and the findings of mammary gland hyperplasia and mammary gland tumors in rats treated with deferiprone in the 52-week toxicology study, tumor formation in carcinogenicity studies must be regarded as likely.

Deferiprone was positive in a mouse lymphoma cell assay in vitro. Deferiprone was clastogenic in an in vitro chromosomal aberration test in mice and in a chromosomal aberration test in Chinese Hamster Ovary cells. Deferiprone given orally or intraperitoneally was clastogenic in a bone marrow micronucleus assay in non-iron-loaded mice. A micronucleus test was also positive when mice predosed with iron dextran were treated with deferiprone. Deferiprone was not mutagenic in the Ames bacterial reverse mutation test.

A fertility and early embryonic development study of deferiprone was conducted in rats. Sperm counts, motility and morphology were unaffected by treatment with deferiprone. There were no effects observed on male or female fertility or reproductive function at the highest dose which was 25% of the MRHD.

14 CLINICAL STUDIES

FERRIPROX Tablets (twice a day) were evaluated in trials in healthy subjects. FERRIPROX Tablets (twice a day) contain deferiprone, the same active ingredient as FERRIPROX Tablets and FERRIPROX Oral Solution. The following information is based on studies with FERRIPROX Tablets (deferiprone) (three times a day) and FERRIPROX Oral Solution (deferiprone).

14.1 Transfusional Iron Overload in Patients with Thalassemia Syndromes

In a prospective, planned, pooled analysis of patients with thalassemia syndromes from several studies, the efficacy of deferiprone was assessed in transfusion-dependent iron overload patients in whom previous iron chelation therapy had failed or was considered inadequate due to poor tolerance. The main criterion for chelation failure was serum ferritin > 2,500 mcg/L before treatment with deferiprone. Deferiprone therapy (35-99 mg/kg/day) was considered successful in individual patients who experienced a ≥ 20% decline in serum ferritin within one year of starting therapy.

Data from a total of 236 patients were analyzed. Of the 224 patients with thalassemia who received deferiprone monotherapy and were eligible for serum ferritin analysis, 105 (47%) were male and 119 (53%) were female. The mean age of these patients was 18.2 years (range 2 to 62; 91 patients were <17).

For the patients in the analysis, the endpoint of at least a 20% reduction in serum ferritin was met in 50% (of 236 subjects), with a 95% confidence interval of 43% to 57%.

A small number of patients with thalassemia and iron overload were assessed by measuring the change in the number of milliseconds (ms) in the cardiac MRI T2* value before and after treatment with deferiprone for one year. There was an increase in cardiac MRI T2* from a mean at baseline of 11.8 ± 4.9 ms to a mean of 15.1 ± 7.0 ms after approximately one year of treatment. The clinical significance of this observation is not known.

14.2 Transfusional Iron Overload in Patients with Sickle Cell Disease and other Anemias

Study LA38-0411, an actively-controlled non-inferiority study compared the efficacy of FERRIPROX to that of deferoxamine in patients with sickle cell disease and other transfusion-dependent anemias by evaluating liver iron concentration (LIC). The efficacy of FERRIPROX was established based upon the change in LIC from baseline after 12 months of FERRIPROX (75 or 99 mg/kg/day) compared to deferoxamine (20 or 40 mg/kg (pediatric patients); 40 or 50 mg/kg (adult patients)). Patient enrollment was stopped following an interim analysis. After adjusting for the type I (alpha) error, the non-inferiority criterion was established as the upper limit of the 96.01% confidence interval for the difference between treatments being ≤2 mg/g dry weight (dw).

Data from 185 patients (122 on FERRIPROX and 63 on deferoxamine) were available. Among the 122 FERRIPROX treated patients, the mean age was 15.9 years (range 3-46); 57.4% were male; 75.4% were White, 17.2% were Black and 7.4% were Multi-racial; 85% were diagnosed with Sickle Cell Disease and 15% with other anemias. Over 12 months, the Least Squares estimate of mean decrease from baseline in LIC was 4.13 ± 0.50 mg/g dw for FERRIPROX and 4.38 ± 0.59 mg/g dw for deferoxamine, and the non-inferiority criterion was met.

Upon completion of the first year of therapy in the non inferiority study, 89 patients from the FERRIPROX group opted to continue with treatment and 45 from the deferoxamine group opted to switch to ferriprox treatment. This group continued for up to an additional 2 years. LIC continued to decrease over time, with the mean value dropping from 14.93 mg/g dw at baseline to 12.30 mg/g dw after one year of treatment, to 11.19 mg/g dw after two years of treatment, and to 10.45 mg/g dw after three years of treatment.

16 HOW SUPPLIED/STORAGE AND HANDLING

FERRIPROX Tablets (twice a day), 1,000 mg

FERRIPROX® Tablets (deferiprone) (twice a day) are white to off-white capsule-shaped, beveled edge, biconvex coated tablets, and have a functional score engraved “FPX” bisect “DR” on one side, “APO” bisect “1000” on the other. They are supplied in child-resistant blister packs or HDPE bottles.

1,000 mg tablets, carton of 5 x 10-count blister packs NDC 10122-104-01

1,000 mg tablets, bottle of 50 tablets NDC 10122-104-05

1,000 mg tablets, bottle of 500 tablets NDC 10122-104-50

Store at 20°C to 25°C (68°F to 77°F); excursions permitted to 15°C to 30°C (59°F to 86°F) [see USP Controlled Room Temperature].

FERRIPROX Tablets (three times a day), 1,000 mg

FERRIPROX® Tablets (deferiprone) (three times a day) are white to off-white capsule-shaped tablets, film-coated, and have a functional score imprinted with “APO” score “1000” on one side and are plain on the other. They are provided in HDPE bottles.

1,000 mg film-coated tablets, 50 tablets NDC 10122-103-05

Store at 20°C to 25°C (68°F to 77°F); excursions permitted to 15°C to 30°C (59°F to 86°F) [see USP Controlled Room Temperature]. Keep the bottle tightly closed to protect from moisture.

17 PATIENT COUNSELING INFORMATION

Advise the patient to read the FDA-approved patient labeling (Medication Guide)

- Instruct patients and their caregivers to store FERRIPROX at 68°F to 77°F (20°C to 25°C); excursions permitted to 59°F to 86°F (15°C to 30°C) [see USP Controlled Room Temperature].
- FERRIPROX Tablets (twice a day), 1,000 mg:
  Advise patients to take the first dose of FERRIPROX Tablets (twice a day) in the morning and the second in the evening.
  Advise patients to take FERRIPROX Tablets (twice a day) with food to reduce the risk of nausea and vomiting.
  Advise patients to avoid alcohol while taking FERRIPROX Tablets (twice a day). Consumption of alcohol while taking FERRIPROX Tablets (twice a day) may result in more rapid release of deferiprone.
- FERRIPROX Tablets (three times a day), 1,000 mg:
  Store in the originally supplied bottle, closed tightly to protect from moisture.
  Advise patients to take the first dose of FERRIPROX in the morning, the second dose at midday, and the third dose in the evening. Clinical experience suggests that taking FERRIPROX with meals may reduce nausea.
- If a dose of this medicine has been missed, take it as soon as possible. However, if it is almost time for the next dose, skip the missed dose and go back to the regular dosing schedule. Do not catch-up or double doses.
- Inform patients of the risks of developing agranulocytosis and the need for regular blood testing before and during their treatment to monitor for decreases in their ANC. Instruct them to immediately interrupt therapy and report to their physician if they experience any symptoms of infection such as fever, sore throat or flu-like symptoms [see Dosage and Administration (2.1) and Warnings and Precautions (5.1)] in order to check their ANC within 24 hours. Advise them if they are unable to reach their physician, seek care from another provider so as not to delay medical care.
- Inform patients of the risk of abnormal liver transaminases and the need for regular blood testing before and during their treatment to monitor for increases in ALT [see Dosage and Administration (2.1) and Warnings and Precautions (5.2)].
- Inform patients of the risk of zinc deficiency and the need for regular blood testing before and during their treatment to monitor for reductions in zinc [see Dosage and Administration (2.1) and Warnings and Precautions (5.3)].
- Advise patients to contact their physician in the event of overdose.
- Inform patients that their urine might show a reddish/brown discoloration due to the excretion of the iron-deferiprone complex. This is a very common sign of the desired effect, and it is not harmful.

Embryo-Fetal toxicity

Advise pregnant women and females of reproductive potential of the potential risk to a fetus. Advise females to inform their healthcare provider of a known or suspected pregnancy [see Warnings and Precautions (5.4) and Use in Specific Populations (8.1)]. Advise female patients of reproductive potential to use effective contraception during treatment with FERRIPROX and for at least six months after the last dose [see Use in Specific Populations (8.1, 8.3)]. Advise males with female partners of reproductive potential to use effective contraception during treatment with FERRIPROX and for at least three months after the last dose [see Use in Specific Populations (8.3) and Nonclinical Toxicology (13.1)].

Lactation

Advise females not to breastfeed during treatment with FERRIPROX and for at least 2 weeks after the last dose [see Use in Specific Populations (8.2)].

Distributed by Chiesi USA, Inc., Cary, NC 27518. Manufactured by Apotex Inc., Toronto, Ontario, Canada, M9L 1T9.

US-618-s1-W

Medication Guide
FERRIPROX (Feh ri prox) Tablets
(deferiprone)

What is the most important information I should know about FERRIPROX Tablets?
FERRIPROX Tablets can cause serious side effects, including a very low white blood cell count. One type of white blood cell that is important for fighting infections is called a neutrophil. If your neutrophil count is low (neutropenia), you may be at risk of developing a serious infection that can lead to death. Neutropenia is common with FERRIPROX Tablets and can become severe in some people. Severe neutropenia is known as agranulocytosis. If you develop agranulocytosis, you will be at risk of developing serious infections that can lead to death.
Your healthcare provider will do a blood test before you start FERRIPROX Tablets and regularly during treatment to check your neutrophil count. If you develop neutropenia, your healthcare provider should check your blood counts every day until your white blood cell count improves. Your healthcare provider may temporarily stop treatment with FERRIPROX Tablets if you develop neutropenia or infection.
Stop taking FERRIPROX Tablets and call your healthcare provider or get medical help right away if you develop any of these symptoms of infection:

- fever
- sore throat or mouth sores
- flu-like symptoms
- chills and severe shaking

It is important for you to have your white blood cell count checked within 24 hours of developing symptoms of an infection to see if you have severe neutropenia (agranulocytosis). Do not delay getting medical care if you are unable to reach your healthcare provider.
See “What are the possible side effects of FERRIPROX Tablets?” for more information about side effects.

What is FERRIPROX Tablets?
FERRIPROX Tablets is a prescription medicine used to treat iron overload from blood transfusions in adults and children 8 years of age and older with:

- thalassemia syndromes.
- sickle cell disease or other anemias.

It is not known if FERRIPROX Tablets is safe and effective to treat iron overload due to blood transfusions:

- in people with myelodysplastic syndrome or Diamond Blackfan anemia
- in children less than 8 years of age

Do not take FERRIPROX Tablets if you are allergic to deferiprone or any of the ingredients in FERRIPROX Tablets. See the end of this Medication Guide for a complete list of ingredients in FERRIPROX Tablets.

Before taking FERRIPROX Tablets, tell your healthcare provider about all of your medical conditions, including if you:

- have liver problems
- are pregnant or plan to become pregnant. FERRIPROX Tablets can harm your unborn baby. You should avoid becoming pregnant during treatment with FERRIPROX Tablets. Tell your healthcare provider right away if you become pregnant or think you may be pregnant during treatment with FERRIPROX Tablets.

Females who are able to become pregnant:
○ Your healthcare provider should do a pregnancy test before you start treatment with FERRIPROX Tablets.
○ You should use effective birth control during treatment with FERRIPROX Tablets and for at least 6 months after the last dose.
Males with female partners who are able to become pregnant:
○ You should use effective birth control during treatment with FERRIPROX Tablets and for at least 3 months after the last dose.

- are breastfeeding or plan to breastfeed. It is not known if FERRIPROX Tablets passes into your breast milk. Do not breastfeed during treatment with FERRIPROX Tablets and for at least 2 weeks after the last dose.

Tell your healthcare provider about all the medicines you take, including prescription and over-the-counter medicines, vitamins and herbal supplements.

How should I take FERRIPROX Tablets?

- Take FERRIPROX Tablets exactly as your healthcare provider tells you.
- Your healthcare provider will prescribe FERRIPROX Tablets based on your body weight.
- Your healthcare provider will check your body iron level during treatment with FERRIPROX Tablets and may change your dose if needed. Your healthcare provider may also change your dose of FERRIPROX Tablets if you have certain side effects. Do not change your dose of FERRIPROX Tablets unless your healthcare provider tells you to.

- There are 2 types of FERRIPROX Tablets that are taken on different schedules. Be sure you are taking the correct tablet and ask your healthcare provider if unsure.

FERRIPROX Tablets
1,000 mg Twice-a-Day
2 times each day with food

FERRIPROX Tablets
1,000 mg
3 times each day

Take your first dose in the morning
and the second dose in the
evening, about 12 hours apart.

Take your first dose in the
morning, the second dose at mid
day, and the third dose in the
evening.

- Taking FERRIPROX Tablets with meals may help reduce nausea.
- If you must take a medicine to treat indigestion (antacid), or supplements that contain iron, aluminum, or zinc during treatment with FERRIPROX Tablets, allow at least 4 hours between taking FERRIPROX Tablets and these products.
- If you take too much FERRIPROX Tablets, call your healthcare provider.
- If you miss a dose, take it as soon as you remember. If it is almost time for your next dose, skip the missed dose and then continue with your regular schedule. Do not try to catch-up or take 2 doses at the same time to make up for a missed dose.

What should I avoid during treatment with FERRIPROX Tablets?

- Avoid drinking alcohol during treatment with FERRIPROX Tablets 1,000 mg (2 times a day). This may cause a faster release of the medicine.

What are the possible side effects of FERRIPROX Tablets?
FERRIPROX Tablets can cause serious side effects, including:

- See “What is the most important information I should know about FERRIPROX Tablets?”
- Increased liver enzyme levels in your blood. Your healthcare provider should do blood tests to check your liver function before you start and then monthly during treatment with FERRIPROX Tablets. Your healthcare provider may temporarily stop treatment with FERRIPROX Tablets if you develop increased liver enzyme levels and they continue to be increased.
- Decreased levels of zinc in your blood. Your healthcare provider will do blood tests to check your zinc levels before you start and during treatment with FERRIPROX Tablets, and may prescribe a zinc supplement for you if your zinc levels are low.

The most common side effects of FERRIPROX Tablets in people with thalassemia include:

- nausea
- joint paint

- vomiting
- abnormal liver function tests

- stomach-area (abdominal) pain
- low white blood cells

The most common side effects of FERRIPROX Tablets in people with sickle cell disease or other anemias include:

- fever
- headache
- sickle cell anemia with crisis
- joint pain
- low white blood cells

- stomach-area (abdominal) pain
- vomiting
- back pain
- mouth and throat pain
- cough

- bone pain
- pain in arms or legs
- abnormal liver function tests
- common cold
- nausea

FERRIPROX Tablets may cause a change in urine color to reddish-brown. This is not harmful and is expected during treatment with FERRIPROX Tablets.
These are not all of the possible side effects of FERRIPROX Tablets.
Call your doctor for medical advice about side effects. You may report side effects to FDA at 1-800-FDA-1088.

How should I store FERRIPROX Tablets?

FERRIPROX Tablets
1,000 mg Twice-a-Day
2 times each day with food

FERRIPROX Tablets
1,000 mg
3 times each day

- Store at room temperature between 68°F to 77°F (20°C to 25°C).

- Store at room temperature between 68°F to 77°F (20°C to 25°C).
- Store in the original bottle and tightly closed to protect from moisture.

Keep FERRIPROX Tablets and all medicines out of the reach of children.

General information about the safe and effective use of FERRIPROX Tablets.
Medicines are sometimes prescribed for purposes other than those listed in a Medication Guide. Do not use FERRIPROX Tablets for a condition for which it was not prescribed. Do not give FERRIPROX Tablets to other people, even if they have the same symptoms that you have. It may harm them. You can ask your pharmacist or healthcare provider for information about FERRIPROX Tablets that is written for health professionals.

What are the ingredients in FERRIPROX Tablets?

FERRIPROX Tablets
1,000 mg Twice-a-Day
2 times each day with food

FERRIPROX Tablets
1,000 mg
3 times each day

Active ingredient: deferiprone
Inactive ingredients: Tablet core: hypromellose acetate succinate, magnesium oxide, colloidal silicon dioxide and magnesium stearate. Coating: triethyl citrate, talc, titanium dioxide, and methacrylic acid and ethyl acrylate copolymer.

Active ingredient: deferiprone
Inactive ingredients: Tablet core: methylcellulose, crospovidone, and magnesium stearate. Coating: hypromellose, hydroxypropyl cellulose, macrogol, and titanium dioxide.

Distributed by: Chiesi USA, Inc., Cary, NC 27518.
Manufactured by: Apotex Inc., Toronto, Ontario, Canada, M9L 1T9.
CTFD-033-0521-00-SPL-1
For more information, call 1-888-661-9260.

This Medication Guide has been approved by the U.S. Food and Drug Administration. Revised:01/2026

PRINCIPAL DISPLAY PANEL

Chiesi USA, Inc. NDC 10122-104-01

Ferriprox (deferiprone) tablets

1,000 mg

Rx only

50 Tablets

PRINCIPAL DISPLAY PANEL

Chiesi USA, Inc. NDC 10122-104-05

Ferriprox (deferiprone) tablets

1,000 mg

Rx only

50 Tablets

PRINCIPAL DISPLAY PANEL

Chiesi USA, Inc. NDC 10122-103-05

Ferriprox (deferiprone) tablets

1,000 mg

Rx only

50 Tablets